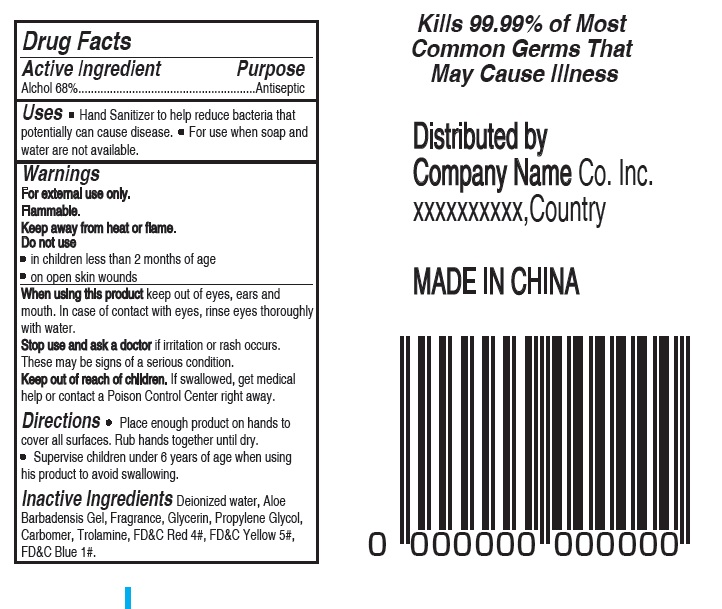 DRUG LABEL: Hand Sanitizer
NDC: 78881-001 | Form: LIQUID
Manufacturer: HANGZHOU AROMA ELECTRONIC COMMERCE CO.,LTD
Category: otc | Type: HUMAN OTC DRUG LABEL
Date: 20200608

ACTIVE INGREDIENTS: ALCOHOL 68 mL/100 mL
INACTIVE INGREDIENTS: POLYACRYLIC ACID (250000 MW); TROLAMINE; WATER; ALOE VERA WHOLE; DIHYDRO PENTAMETHYLINDANONE; GLYCERIN; PROPYLENE GLYCOL

HAND SANITIZER

Active Ingredient

Alcohol 68% Purpose: Antiseptic

Purpose

Antiseptic

Use

Hand Sanitizer to help reduce bacteria that potentially can cause disease. For use when soap and water are not available.

Warnings

For external use only. Flammable. Keep away from heat or flame

Do not use

- in children less than 2 months of age
- on open skin wounds

When using this product keep out of eyes, ears, and mouth. In case of contact with eyes, rinse eyes thoroughly with water.
Stop use and ask a doctor if irritation or rash occurs. These may be signs of a serious condition.
Keep out of reach of children. If swallowed, get medical help or contact a Poison Control Center right away.

Stop use and ask a doctor if irritation or rash occurs. These may be signs of a serious condition.

Keep out of reach of children. If swallowed, get medical help or contact a Poison Control Center right away.

Directions

- Place enough product on hands to cover all surfaces. Rub hands together until dry.
- Supervise children under 6 years of age when using this product to avoid swallowing.

Inactive ingredients

Deionized water,Aloe Barbadensis Gel,Fragrance,Glycerin,Propylene Glycol,Carbomer,Trolamine,FD&C Red 4#,FD&C Yellow 5#,FD&C Blue 1#.